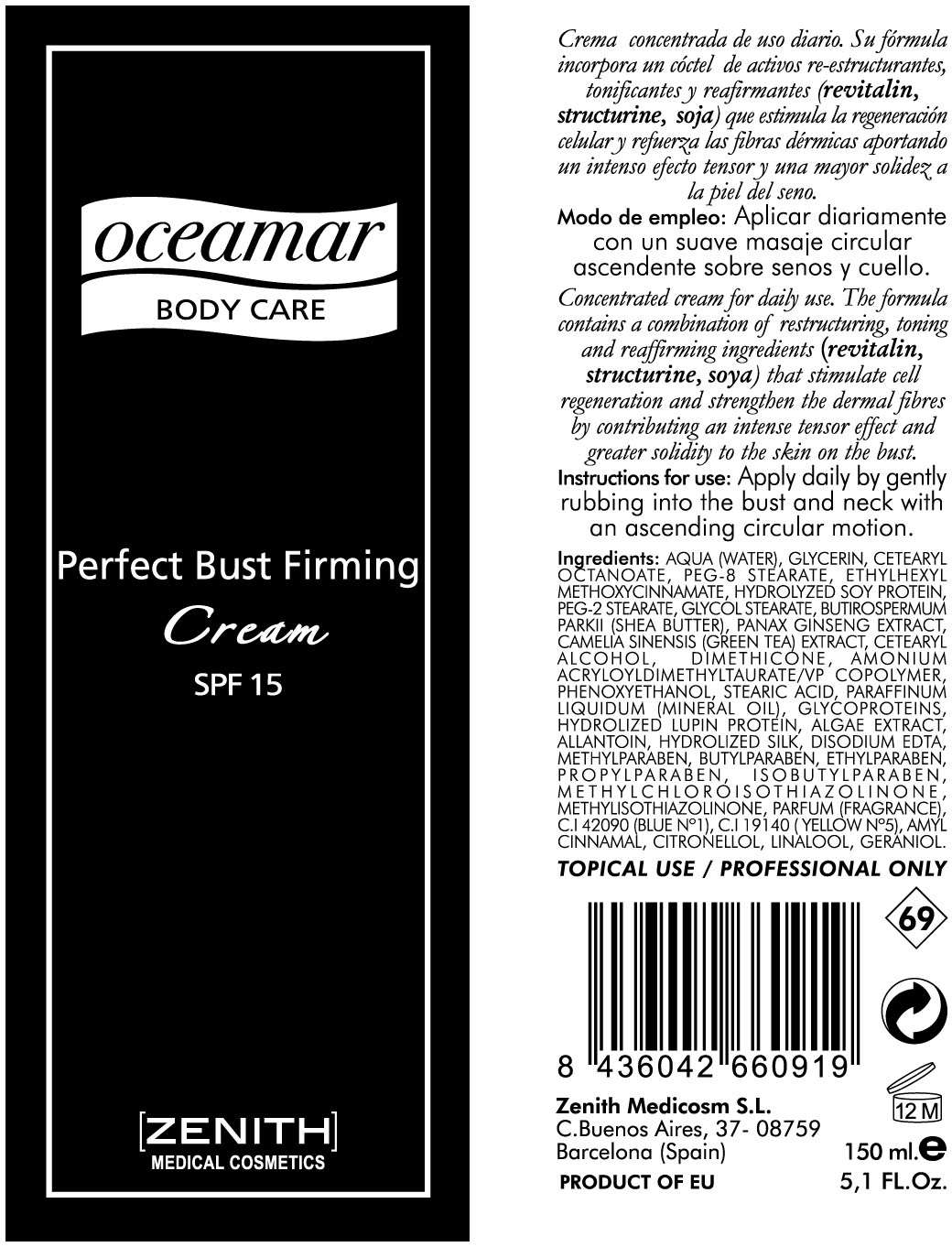 DRUG LABEL: PERFECT BUST
NDC: 42248-131 | Form: CREAM
Manufacturer: Zenith Medicosm SL
Category: otc | Type: HUMAN OTC DRUG LABEL
Date: 20120523

ACTIVE INGREDIENTS: OCTINOXATE 11.25 mL/150 mL
INACTIVE INGREDIENTS: PEG-2 STEARATE; PROPYLPARABEN; METHYLPARABEN; GREEN TEA LEAF; CETEARYL ETHYLHEXANOATE; ASIAN GINSENG; WATER; AMMONIUM ACRYLOYLDIMETHYLTAURATE; STEARIC ACID; SOY PROTEIN; SHEA BUTTER; LAMINARIA DIGITATA; HYDROLYZED WHEAT PROTEIN (ENZYMATIC, 3000 MW); GREEN TEA LEAF; MINERAL OIL; METHYLISOTHIAZOLINONE; PHENOXYETHANOL; GERANIOL; METHYLPARABEN; ISOBUTYLPARABEN; ALLANTOIN; LINALOOL, (+/-)-; BUTYLPARABEN; ETHYLPARABEN; CETOSTEARYL ALCOHOL; .BETA.-CITRONELLOL, (R)-; .ALPHA.-AMYLCINNAMALDEHYDE; EDETIC ACID; DIMETHICONE; BOMBYX MORI FIBER; FD&C BLUE NO. 1; FD&C YELLOW NO. 5

Drug Facts

Active Ingredient

Octinoxate 7.5%

Description

PERFECT BUST FIRMING CREAM

SPF 15

Concentrated cream for daily use. The formula contains a combination of restructuring, toning and reaffirming ingredients (revitalin, structurine, soy) that stimulate cell regeneration and strenghten the dermal fibers by contributing an intense tensor effect and greater solidity to the skin on the bust.

150ml. 5.1Fl.Oz.

Warning

TOPICAL USE / PROFESSIONAL ONLY

Instructions for use

Apply daily by gently rubbing into the bust and neck with an ascending circular motion.